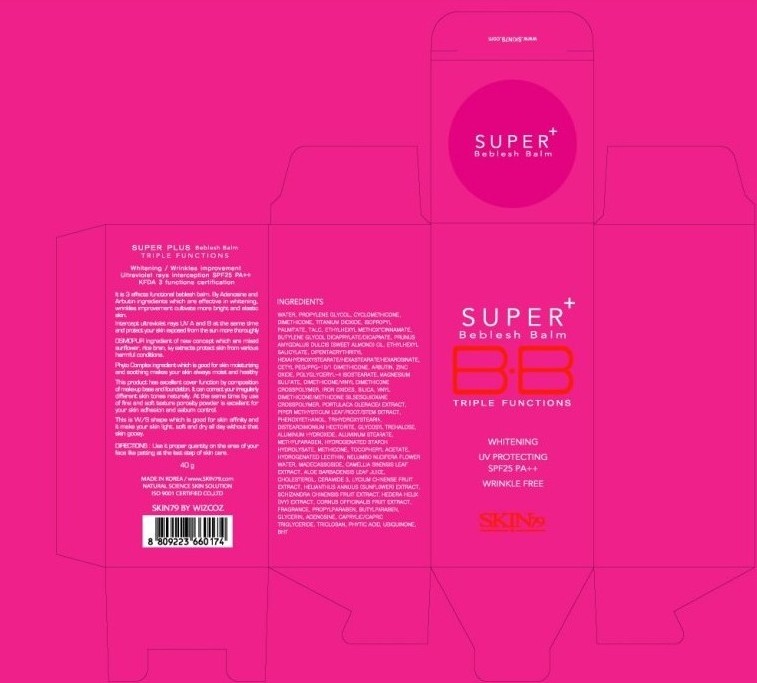 DRUG LABEL: SKIN 79 Super Plus Beblesh Balm Triple Functions SPF25 PA (40g)
NDC: 49715-005 | Form: CREAM
Manufacturer: WIZCOZ CORPORATION LTD
Category: otc | Type: HUMAN OTC DRUG LABEL
Date: 20091109

ACTIVE INGREDIENTS: ZINC OXIDE 0.78 g/40 g; OCTISALATE 0.8 g/40 g; OCTINOXATE 1.2 g/40 g; TITANIUM DIOXIDE 1.92 g/40 g
INACTIVE INGREDIENTS: DIMETHICONE 2.2 g/40 g; ALUMINUM HYDROXIDE 0.072 g/40 g

ACTIVE INGREDIENT

INGREDIENTS:

WATER, PROPYLENE GLYCOL, CYCLOMETHICONE, DIMETHICONE, TITANIUM DIOXIDE, ISOPROPYL PALMITATE, TALC, ETHYLHEXYL METHOXYCINNAMATE, BUTYLENE GLYCOL DICAPRYLATE/DICAPRATE, PRUNUS AMYGDALUS DIACIS (SWEET ALMOND) OIL, ETHYLHEXYL SALICYLATE, DIPENTAERYTHRITYL HEXAHYDROXYSTEARATE/HEXASTEARATE/HEXAROSINATE, CETYL PEG/PPG-10/1 DIMETHICONE, ARBUTIN, ZINC OXIDE, POLYGLYCERYL-4 ISOSTEARATE, MAGNESIUM SULFATE, DIMETHICONE/VINYL DIMETHICONE CROSSPOLYMER, IRON OXIDES, SILICA, VINYL DIMETHICONE/METHICONE SISSESQUIOXANE CROSSPOLYER, PORTULACA OLERACEA EXTRACT, PIPER METHYSTICUM LEAF/ROOT/STEM EXTRACT, PHENOSYETHANOL, TRIHYDROXYSTEARIN, DISTEARDIMONIUM HECTORITE, GLYCOSYL TREMALOSE, ALUMINUM HYDROXIDE, ALUMINUM STEARATE, METHYLPARABEN, HYDROGENATED STARCH HYDROLYSATE, METHICONE, TOCOPHEYL ACETATE, HYDROGENATED LECITHIN, NELUMBO NUCIFERA FLOWER WATER, MADECASSOSIDE, CAMELLIA SINENSIS LEAF EXTRACT, ALOE BARBEDENSIS LEAF JUICE, CHOLESTEROL, CERAMIDE 3, LYCIUM CHINENSE FRUTI EXTRACT, HELIANTHUS ANNUUS (SUNFLOWER) EXTRACT, SCHIZANDRA CHINENSIS FRUIT EXTRACT, HEDERA HELIX (IVY) EXTRACT, CORNUS OFFICINALIS FRUIT EXTRACT, FRAGRANCE, PROPYLPARABEN, BUTYLPARABEN, GLYCERIN, ADENOSINE, CAPRYLIC/CAPRIC TRIGLYCERIDE, TRICLOSAN, PHYTIC ACID, UBIQUINONE, BHT

DIRECTIONS:

Use it proper quantity on the area of your face like patting at the last step of skin care.